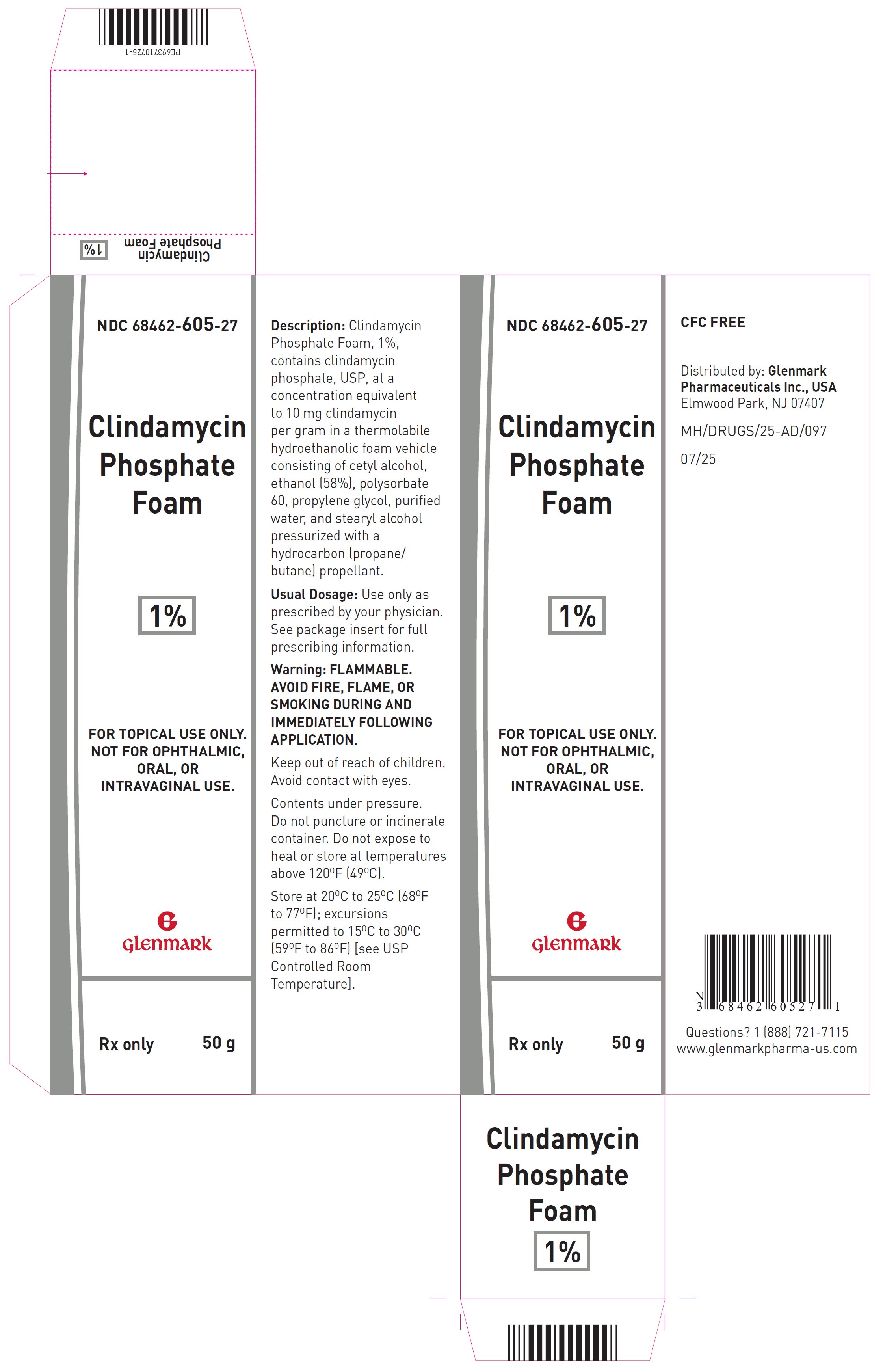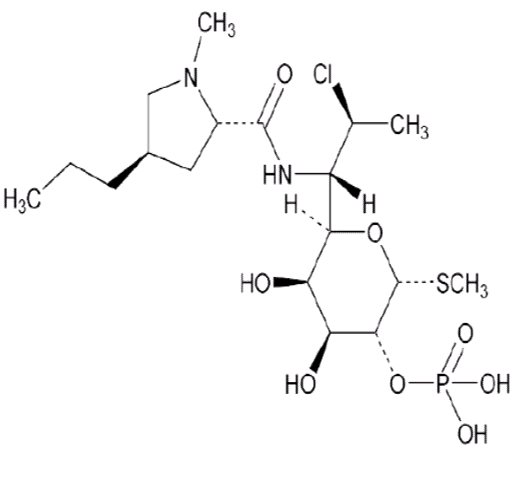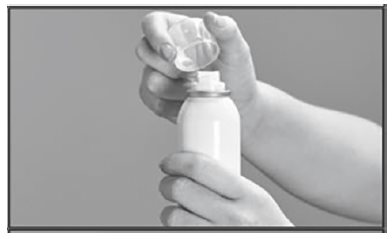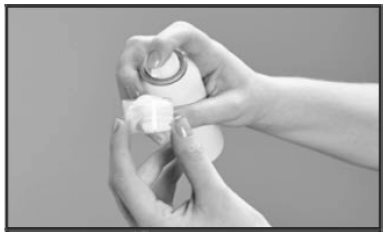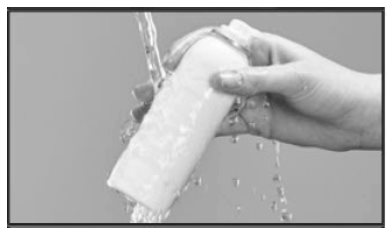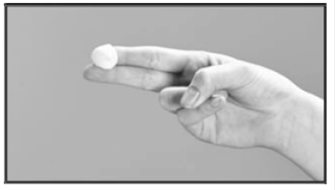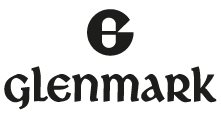 DRUG LABEL: Clindamycin Phosphate
NDC: 68462-605 | Form: AEROSOL, FOAM
Manufacturer: GLENMARK PHARMACEUTICALS INC., USA
Category: prescription | Type: HUMAN PRESCRIPTION DRUG LABEL
Date: 20260129

ACTIVE INGREDIENTS: CLINDAMYCIN PHOSPHATE 10 mg/1 g
INACTIVE INGREDIENTS: CETYL ALCOHOL; ALCOHOL; POLYSORBATE 60; PROPYLENE GLYCOL; WATER; STEARYL ALCOHOL

HIGHLIGHTS OF PRESCRIBING INFORMATION

These highlights do not include all the information needed to use CLINDAMYCIN PHOSPHATE FOAM safely and effectively. See full prescribing information for CLINDAMYCIN PHOSPHATE FOAM.
CLINDAMYCIN PHOSPHATE foam, for topical use
Initial U.S. Approval: 1970

1 INDICATIONS AND USAGE

Clindamycin phosphate foam is a lincosamide product indicated for acne vulgaris in patients 12 years and older. (1)

2 DOSAGE AND ADMINISTRATION

- For topical use only; not for oral, ophthalmic, or intravaginal use. (2)
- Apply clindamycin phosphate foam once daily to affected areas. (2)
- Flammable; avoid fire, flame and/or smoking during and immediately following application. (2)

3 DOSAGE FORMS AND STRENGTHS

Foam containing 1% clindamycin as clindamycin phosphate, USP. (3)

4 CONTRAINDICATIONS

Clindamycin phosphate foam is contraindicated in individuals with a history of regional enteritis or ulcerative colitis, or a history of antibiotic-associated colitis (including pseudomembranous colitis). (4)

5 WARNINGS AND PRECAUTIONS

- Colitis: Clindamycin can cause severe colitis, which may result in death. Diarrhea, bloody diarrhea, and colitis (including pseudomembranous colitis) have been reported with the use of clindamycin. Clindamycin phosphate foam should be discontinued if significant diarrhea occurs. (5.1)

6 ADVERSE REACTIONS

The most common adverse reactions (>1%) are headache and application site reactions including burning, pruritus, and dryness. (6.1)

To report SUSPECTED ADVERSE REACTIONS, contact Glenmark Pharmaceuticals Inc., USA at 1 (888) 721-7115 or FDA at 1-800-FDA-1088 or www.fda.gov/medwatch.

FULL PRESCRIBING INFORMATION

1 INDICATIONS AND USAGE

Clindamycin phosphate foam is indicated for topical application in the treatment of acne vulgaris in patients 12 years and older.

2 DOSAGE AND ADMINISTRATION

Clindamycin phosphate foam is for topical use only, and not for oral, ophthalmic, or intravaginal use.

Apply clindamycin phosphate foam once daily to affected areas after the skin is washed with mild soap and allowed to fully dry. Use enough to cover the entire affected area.

If there has been no improvement after 6 to 8 weeks or if the condition becomes worse, treatment should be discontinued.

The contents of clindamycin phosphate foam are flammable; avoid fire, flame and/or smoking during and immediately following application.

3 DOSAGE FORMS AND STRENGTHS

Clindamycin Phosphate Foam is a white thermolabile hydroethanolic aerosol foam. Each gram of clindamycin phosphate foam contains, as dispensed, 12 mg (1.2%) of clindamycin phosphate, USP equivalent to 10 mg (1%) of clindamycin.

4 CONTRAINDICATIONS

Clindamycin phosphate foam is contraindicated in individuals with a history of regional enteritis or ulcerative colitis, or a history of antibiotic-associated colitis (including pseudomembranous colitis).

5 WARNINGS AND PRECAUTIONS

5.1 Colitis

Systemic absorption of clindamycin has been demonstrated following topical use of this product. Diarrhea, bloody diarrhea, and colitis (including pseudomembranous colitis) have been reported with the use of topical clindamycin. If significant diarrhea occurs, clindamycin phosphate foam should be discontinued [see Adverse Reactions (6.2)].

Severe colitis has occurred following oral or parenteral administration of clindamycin with an onset of up to several weeks following cessation of therapy. Antiperistaltic agents such as opiates and diphenoxylate with atropine may prolong and/or worsen severe colitis. Severe colitis may result in death.

Studies indicate a toxin(s) produced by Clostridia is one primary cause of antibiotic-associated colitis. The colitis is usually characterized by severe persistent diarrhea and severe abdominal cramps and may be associated with the passage of blood and mucus. Stool cultures for Clostridium difficile and stool assay for C. difficile toxin may be helpful diagnostically.

5.2 Irritation

Clindamycin phosphate foam can cause irritation. Concomitant topical acne therapy should be used with caution since a possible cumulative irritancy effect may occur, especially with the use of peeling, desquamating, or abrasive agents. If irritation or dermatitis occurs, clindamycin should be discontinued.

Avoid contact of clindamycin phosphate foam with eyes, mouth, lips, other mucous membranes or areas of broken skin. If contact occurs, rinse thoroughly with water.

Clindamycin phosphate foam should be prescribed with caution in atopic individuals.

6 ADVERSE REACTIONS

6.1 Clinical Trials Experience

Because clinical trials are conducted under widely varying conditions, adverse reaction rates observed in the clinical trials of a drug cannot be directly compared to rates in the clinical trials of another drug and may not reflect the rates observed in clinical practice.

A total of 439 subjects with mild to moderate acne vulgaris were treated once daily for 12 weeks with clindamycin phosphate foam.

The incidence of adverse reactions occurring in ≥ 1% of the subjects in clinical trials comparing clindamycin phosphate foam and its vehicle is presented in Table 1.

Table 1: Adverse Reactions Occurring in ≥ 1% of Subjects
Adverse Reactions | Number (%) of Subjects
 | Clindamycin Phosphate Foam | Vehicle Foam
 | N = 439 | N = 154
Headache | 12 (3%) | 1 (1%)
Application site burning | 27 (6%) | 14 (9%)
Application site pruritus | 5 (1%) | 5 (3%)
Application site dryness | 4 (1%) | 5 (3%)
Application site reaction, not otherwise specified | 3 (1%) | 4 (3%)

In a contact sensitization study, none of the 203 subjects developed evidence of allergic contact sensitization to clindamycin phosphate foam.

6.2 Postmarketing Experience

The following adverse reactions have been identified during post approval use of clindamycin phosphate foam: application site pain, application site erythema, diarrhea, urticaria, abdominal pain, hypersensitivity, rash, abdominal discomfort, nausea, seborrhea, application site rash, dizziness, pain of skin, colitis (including pseudomembranous colitis), and hemorrhagic diarrhea. Because these reactions are reported voluntarily from a population of uncertain size, it is not always possible to reliably estimate their frequency or establish a causal relationship to drug exposure.

Abdominal pain and gastrointestinal disturbances, as well as gram-negative folliculitis, have also been reported in association with the use of topical formulations of clindamycin. Orally and parenterally administered clindamycin have been associated with severe colitis, which may end fatally.

7 DRUG INTERACTIONS

7.1 Erythromycin

Clindamycin phosphate foam should not be used in combination with topical or oral erythromycin-containing products due to possible antagonism to its clindamycin component. In vitro studies have shown antagonism between these two antimicrobials. The clinical significance of this in vitro antagonism is not known.

7.2 Neuromuscular Blocking Agents

Clindamycin has been shown to have neuromuscular blocking properties that may enhance the action of other neuromuscular blocking agents. Therefore, clindamycin phosphate foam should be used with caution in patients receiving such agents.

8 USE IN SPECIFIC POPULATIONS

8.1 Pregnancy

Risk Summary

There are no available data on clindamycin phosphate foam use in pregnant women to inform a drug-associated risk for adverse developmental outcomes.

Animal reproduction studies have not been conducted with clindamycin phosphate foam. No evidence of fetal harm or malformations was observed in pregnant rats and mice administered daily subcutaneous or oral doses of clindamycin salts during organogenesis at doses that produced exposures up to 84 and 42 times, respectively, the maximum recommended human dose (MRHD) of clindamycin phosphate foam based on body surface area (BSA) comparisons and assuming 100% absorption [see Data].

In the U.S. general population, the estimated background risk of major birth defects and miscarriage in clinically recognized pregnancies is 2 to 4% and 15 to 20%, respectively.

Data

Animal Data

Reproduction studies have been conducted in rats and mice using subcutaneous or oral doses of clindamycin phosphate, clindamycin hydrochloride or clindamycin palmitate hydrochloride administered daily during organogenesis at doses up to the equivalent of 432 mg/kg/day clindamycin phosphate. These studies produced no evidence of fetal harm or malformations in rats or mice at exposures 84 or 42 times, respectively, the MRHD of clindamycin phosphate (i.e., 5 milliliters of clindamycin phosphate foam) based on BSA comparison and assuming 100% absorption.

8.2 Lactation

Risk Summary

There is no information on the presence of clindamycin in human milk, or the effects on the breast-fed child, or the effects on milk production following use of clindamycin phosphate foam. However, orally and parenterally administered clindamycin has been reported to appear in breast milk.

The developmental and health benefits of breastfeeding should be considered along with the mother’s clinical need for clindamycin phosphate foam and any potential adverse effects on the breast-fed child from clindamycin phosphate foam or from the underlying maternal condition.

Clinical Considerations

If used during lactation and clindamycin phosphate foam is applied to the chest, care should be taken to avoid accidental ingestion by the infant.

8.4 Pediatric Use

Safety and effectiveness of clindamycin phosphate foam in children under the age of 12 have not been studied.

8.5 Geriatric Use

The clinical study with clindamycin phosphate foam did not include sufficient numbers of subjects aged 65 and over to determine if they respond differently than younger subjects.

11 DESCRIPTION

Clindamycin Phosphate Foam contains clindamycin (1%) as clindamycin phosphate, USP.

Clindamycin phosphate, USP is a water-soluble ester of the semi-synthetic antibiotic produced by a 7(S)-chloro-substitution of the 7(R)-hydroxyl group of the parent antibiotic, lincomycin.

The chemical name for clindamycin phosphate, USP is methyl 7-chloro-6,7,8-trideoxy-6-(1-methyl-trans-4-propyl-L-2-pyrrolidinecarboxamido)-1-thio-L-threo-α-D-galacto-octopyranoside 2-(dihydrogen phosphate). The structural formula for clindamycin phosphate, USP is represented below:

Molecular Formula: C18H34ClN2O8PS Molecular Weight: 504.96 g/mol

Clindamycin Phosphate Foam contains clindamycin (1%) as clindamycin phosphate, USP at a concentration equivalent to 10 mg clindamycin per gram in a thermolabile hydroethanolic foam vehicle consisting of cetyl alcohol, ethanol (58%), polysorbate 60, propylene glycol, purified water, and stearyl alcohol pressurized with a hydrocarbon (propane/butane) propellant.

12 CLINICAL PHARMACOLOGY

12.1 Mechanism of Action

Mechanism of action of clindamycin in acne vulgaris is unknown [see Microbiology (12.4)].

12.2 Pharmacodynamics

Pharmacodynamics of clindamycin phosphate foam is unknown.

12.3 Pharmacokinetics

In an open label, parallel group study in 24 subjects with acne vulgaris, 12 subjects (3 male and 9 female) applied 4 grams of clindamycin phosphate foam once-daily for five days, and 12 subjects (7 male and 5 female) applied 4 grams of a clindamycin gel, 1%, once daily for five days. On Day 5, the mean Cmax and AUC(0 to 12) were 23% and 9% lower, respectively, for clindamycin phosphate foam than for the clindamycin gel, 1%.

Following multiple applications of clindamycin phosphate foam, less than 0.024% of the total dose was excreted unchanged in the urine over 12 hours on Day 5.

12.4 Microbiology

No microbiology studies were conducted in the clinical trials with this product.

Clindamycin binds to the 50S ribosomal subunits of susceptible bacteria and prevents elongation of peptide chains by interfering with peptidyl transfer, thereby suppressing protein synthesis. Clindamycin has been shown to have in vitro activity against Propionibacterium acnes (P. acnes), an organism that has been associated with acne vulgaris; however, the clinical significance of this activity against P. acnes was not examined in clinical studies with clindamycin phosphate foam. P. acnes resistance to clindamycin has been documented.

Inducible Clindamycin Resistance

The treatment of acne with antimicrobials is associated with the development of antimicrobial resistance in P. acnes as well as other bacteria (e.g. Staphylococcus aureus, Streptococcus pyogenes). The use of clindamycin may result in developing inducible resistance in these organisms. This resistance is not detected by routine susceptibility testing.

Cross Resistance:

Resistance to clindamycin is often associated with resistance to erythromycin.

13 NONCLINICAL TOXICOLOGY

13.1 Carcinogenesis, Mutagenesis, Impairment of Fertility

The carcinogenicity of a 1.2% clindamycin phosphate gel similar to clindamycin phosphate foam was evaluated by daily topical administration to mice for two years. The topical doses used in this study were approximately 3 and 15 times higher than the MRHD of clindamycin phosphate from clindamycin phosphate foam, based on BSA comparison and assuming 100% absorption. No significant increase in tumors was noted in the treated animals.

The genotoxic potential of clindamycin was evaluated in an in vitro Ames assay and in an in vivo rat micronucleus test. Both tests were negative.

Reproduction studies in rats using oral doses of clindamycin hydrochloride or clindamycin palmitate hydrochloride have revealed no evidence of impaired fertility.

14 CLINICAL STUDIES

In one multicenter, randomized, double-blind, vehicle-controlled clinical trial, subjects with mild to moderate acne vulgaris used clindamycin phosphate foam or the vehicle foam once daily for twelve weeks. Treatment response, defined as the proportion of subjects clear or almost clear, based on the Investigator Static Global Assessment (ISGA), and the mean percent reductions in lesion counts at the end of treatment in this study are shown in Table 2.

Table 2: Efficacy Results at Week 12
Efficacy Parameters | Clindamycin Phosphate Foam; N=386 | Vehicle Foam; N=127
Treatment response (ISGA) | 31% | 18%*
Percent reduction in lesion counts
Inflammatory Lesions | 49% | 35%*
Noninflammatory Lesions | 38% | 27%*
Total Lesions | 43% | 31%*
*P < 0.05

16 HOW SUPPLIED/STORAGE AND HANDLING

16.1 How Supplied

Clindamycin Phosphate Foam, 1% contains clindamycin phosphate, USP equivalent to 10 mg clindamycin per gram. The white thermolabile hydroethanolic aerosol foam is available as follows.

100 gram aerosol can - NDC 68462-605-94

50 gram aerosol can - NDC 68462-605-27

16.2 Storage and Handling

Store at 20°C to 25°C (68°F to 77°F); excursions permitted to 15°C to 30°C (59°F to 86°F) [see USP Controlled Room Temperature].

Flammable. Avoid fire, flame or smoking during and immediately following application.

Contents under pressure. Do not puncture or incinerate. Do not expose to heat or store at temperature above 120°F (49°C).

Keep out of reach of children.

17 PATIENT COUNSELING INFORMATION

See FDA-Approved patient labeling (Patient Information).

17.1 Instructions for Use

- Patients should be advised to wash their skin with mild soap and allow it to dry before applying clindamycin phosphate foam.
- Patients should use enough clindamycin phosphate foam to cover the face and to apply once daily.
- Patients should dispense clindamycin phosphate foam directly into the cap or onto a cool surface.
- Patients should wash their hands after applying clindamycin phosphate foam.

17.2 Skin Irritation

Clindamycin phosphate foam may cause irritation such as erythema, scaling, itching, burning, or stinging. Patients should be advised to discontinue use if excessive irritancy or dermatitis occur.

17.3 Colitis

In the event a patient treated with clindamycin phosphate foam experiences severe diarrhea or gastrointestinal discomfort, clindamycin phosphate foam should be discontinued and a physician should be contacted.

Distributed by:

Glenmark Pharmaceuticals Inc., USA

Elmwood Park, NJ 07407

Questions? 1 (888) 721-7115

www.glenmarkpharma-us.com

July 2025

PATIENT INFORMATION

Clindamycin Phosphate

(kiln-da-MYE-sin-fos-fate)

Foam, 1%

Important Information: Clindamycin phosphate foam is for use on the skin only. Do not use clindamycin phosphate foam in your eyes, mouth or vagina.

What is Clindamycin Phosphate Foam?

Clindamycin phosphate foam is a prescription medicine used on the skin (topical) to treat acne vulgaris in people 12 years and older.

It is not known if clindamycin phosphate foam is safe and effective in children under 12 years of age.

Who should not use Clindamycin Phosphate Foam?

Do not use clindamycin phosphate foam if you:

- have Crohn’s disease
- have ulcerative colitis
- have had inflammation of the colon (colitis) or severe diarrhea with past antibiotic use

Tell your doctor if you are not sure if you have any of the conditions listed above.

What should I tell my doctor before using Clindamycin Phosphate Foam?

Before using clindamycin phosphate foam, tell your doctor about all of your medical conditions, including if you:

- have or have had bowel problems (such as Crohn’s disease, ulcerative colitis, colitis)
- have or have had eczema or other skin problems.
- are planning to have surgery. Clindamycin phosphate foam may affect how certain medicines work that may be given during surgery.
- are pregnant or plan to become pregnant. It is not known if clindamycin phosphate foam may harm your unborn baby.
- are breastfeeding or plan to breastfeed. It is not known if clindamycin phosphate passes into your breast milk. Talk to your doctor about using clindamycin phosphate foam while breastfeeding. If you use clindamycin phosphate foam while breastfeeding and clindamycin phosphate foam is applied on the chest, take care to avoid getting clindamycin phosphate foam into your baby’s mouth.

Tell your doctor about all the medicines you take including prescription and over-the-counter medicines, vitamins and herbal supplements.

Clindamycin phosphate foam may affect the way other medicines work and other medicines may affect how clindamycin phosphate foam works.

Especially tell your doctor if you take medicine by mouth that contains erythromycin or use products on your skin that contain erythromycin.

Know the medicines you take. Keep a list of them to show your doctor and pharmacist when you get a new medicine.

How should I use Clindamycin Phosphate Foam?

- Use clindamycin phosphate foam exactly as your doctor tells you to use it. See the detailed “Instructions for Use” for directions about how to apply clindamycin phosphate foam correctly.
- Wash your skin with mild soap and water and dry before applying clindamycin phosphate foam.
- Apply clindamycin phosphate foam 1 time each day to the affected skin area. You should apply enough clindamycin phosphate foam to cover the entire affected area.
- Dispense clindamycin phosphate foam directly into the cap. Do not dispense clindamycin phosphate foam directly onto your hands or face, because the foam will begin to melt on contact with warm skin.
- Wash your hands after applying clindamycin phosphate foam.

What should I avoid while using Clindamycin Phosphate Foam?

- Clindamycin phosphate foam is flammable. Avoid fire, flames, or smoking during and right after you apply clindamycin phosphate foam to your skin.
- Avoid getting clindamycin phosphate foam in or near your eyes, mouth, lips, or broken skin. If you get clindamycin phosphate foam in your eyes, mouth, on lips or broken skin, rinse well with water.

What are possible side effects with Clindamycin Phosphate Foam?

Clindamycin phosphate foam may cause serious side effects, including:

- Inflammation of the colon (colitis). Diarrhea, bloody diarrhea, and colitis has happened in people who use clindamycin phosphate foam. Stop using clindamycin phosphate foam and call your doctor right away if you have severe stomach (abdominal) cramps, watery diarrhea, or bloody diarrhea during treatment, and for several weeks after treatment, with clindamycin phosphate foam.
- Skin irritation. Stop using clindamycin phosphate foam and call your doctor if you develop skin irritation during treatment with clindamycin phosphate foam.

The most common side effects of clindamycin phosphate foam include headache and application site reactions (including burning, itching, and dryness).

These are not all the possible side effects of clindamycin phosphate foam.

Call your doctor for medical advice about side effects. You may report side effects to FDA at 1-800-FDA-1088. You may report side effects to Glenmark Pharmaceuticals Inc., USA at 1(888)-721-7115.

How should I store Clindamycin Phosphate Foam?

- Store clindamycin phosphate foam at room temperature between 68°F to 77°F (20°C to 25°C).
- Keep clindamycin phosphate foam away from heat. Never throw the can into a fire, even if the can is empty.
- Do not store clindamycin phosphate foam at temperatures above 120°F (49°C).
- Do not break through (puncture) the clindamycin phosphate foam can.

Keep clindamycin phosphate foam and all medicines out of the reach of children.

General information about the safe and effective use of Clindamycin Phosphate Foam:

Medicines are sometimes prescribed for purposes other than those listed in Patient Information leaflet. Do not use clindamycin phosphate foam for a condition for which it was not prescribed. Do not give clindamycin phosphate foam to other people, even if they have the same symptoms you have. It may harm them. You can also ask your pharmacist or doctor for information about clindamycin phosphate foam that is written for health professionals.

What are the ingredients in Clindamycin Phosphate Foam?

Active ingredient: clindamycin phosphate

Inactive ingredients: cetyl alcohol, ethanol (58%), polysorbate 60, propylene glycol, purified water, and stearyl alcohol. The can is pressurized with a hydrocarbon (propane/butane) propellant.

This Patient Information has been approved by the U.S. Food and Drug Administration.

Distributed by:

Glenmark Pharmaceuticals Inc., USA

Elmwood Park, NJ 07407

Questions? 1 (888) 721-7115

www.glenmarkpharma-us.com

July 2025

Instructions for Use

Clindamycin Phosphate

(klin-da-MYE-sin fos-fate)

Foam, 1%

Important Information: Clindamycin phosphate foam is for use on the skin only. Do not use clindamycin phosphate foam in your eyes, mouth or vagina.

Step 1: Remove the clear cap from the clindamycin phosphate foam can.

Step 2: Hold the can upright and firmly press the nozzle to dispense clindamycin phosphate foam into the clear cap.

- Dispense enough clindamycin phosphate foam to cover the entire affected area.

- If the can seems warm or the foam seems runny, run the can under cold water.

Step 3: Pick up small amounts of clindamycin phosphate foam with your fingertips and gently rub the foam into the affected area until the foam disappears.

Step 4: Wash your hands after applying clindamycin phosphate foam.

Throw away any of the unused medicine that you dispensed out of the can.

How should I store clindamycin phosphate foam?

- Store clindamycin phosphate foam at room temperature between 68°F to 77°F (20°C to 25°C).
- Keep clindamycin phosphate foam away from heat. Never throw the can into a fire, even if the can is empty.
- Do not store clindamycin phosphate foam at temperatures above 120°F (49°C).
- Do not break through (puncture) the clindamycin phosphate foam can.

Keep clindamycin phosphate foam and all medicines out of the reach of children.

The Patient Information and Instructions for Use have been approved by the U.S. Food and Drug Administration.

Distributed by:

Glenmark Pharmaceuticals Inc., USA

Elmwood Park, NJ 07407

Questions? 1 (888) 721-7115

www.glenmarkpharma-us.com

July 2025

PACKAGE LABEL

Principal Display Panel